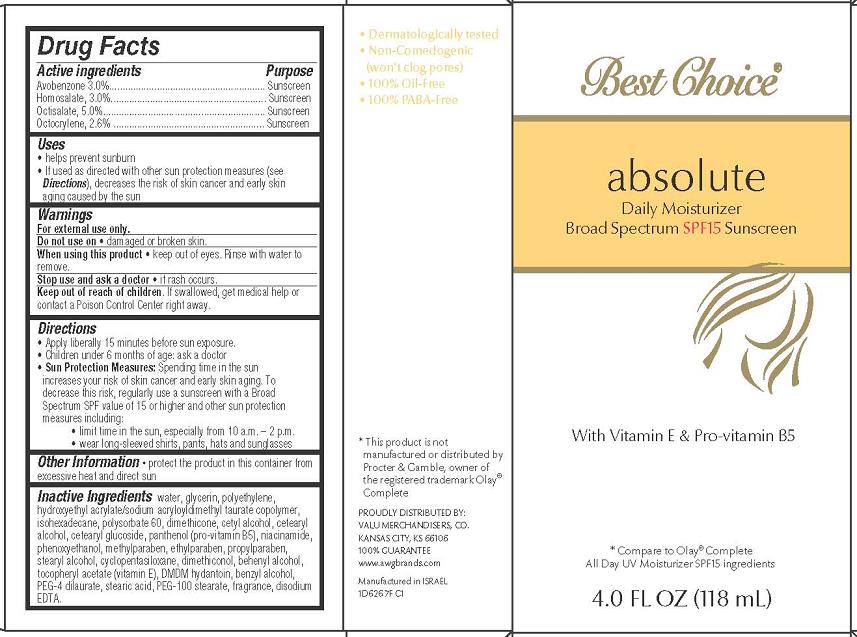 DRUG LABEL: Best Choice absolute Daily Moisturizing Broad Spectrum SPF 15 Sunscreen
NDC: 63941-626 | Form: CREAM
Manufacturer: Valu Merchandisers Company
Category: otc | Type: HUMAN OTC DRUG LABEL
Date: 20130206

ACTIVE INGREDIENTS: AVOBENZONE 20 mg/1 mL; OCTOCRYLENE 26 mg/1 mL; HOMOSALATE 30 mg/1 mL; OCTINOXATE 50 mg/1 mL
INACTIVE INGREDIENTS: WATER; GLYCERIN; POLYETHYLENE GLYCOLS; HYDROXYETHYL ACRYLATE/SODIUM ACRYLOYLDIMETHYL TAURATE COPOLYMER (45000 MPA.S AT 1%); ISOHEXADECANE; POLYSORBATE 60; DIMETHICONE; CETYL ALCOHOL; CETOSTEARYL ALCOHOL; CETEARYL GLUCOSIDE; PANTHENOL; NIACINAMIDE; PHENOXYETHANOL; METHYLPARABEN; ETHYLPARABEN; PROPYLPARABEN; STEARYL ALCOHOL; CYCLOMETHICONE 5; DIMETHICONOL (100000 CST); DOCOSANOL; .ALPHA.-TOCOPHEROL ACETATE; DMDM HYDANTOIN; BENZYL ALCOHOL; PEG-4 DILAURATE; STEARIC ACID; PEG-100 STEARATE; EDETATE DISODIUM

Best Choice® absolute Daily Moisturizing Broad Spectrum SPF 15 Sunscreen

Active ingredient

Avobenzone 3.0%

Homosalate 3.0%

Octisalate 5.0%

Octocrylene 2.6%

Purpose

Sunscreen

Keep Out of Reach of Children

If swallowed, get medical help or contact a Poison Control Center right away.

Uses

- help prevent sunburn
- If used as directed with other sun protection measures (see Directions), decreases the risk of skin cancer and early skin aging caused by the sun

Warnings

For external use only.

Do not use on damaged or broken skin.

When using this product keep out of eyes. Rinse with water to remove.

Stop use and ask a doctor if rash occurs.

Directions

Apply liberally 15 minutes before sun exposure.

Children under 6 months of age: ask a doctor

Sun Protection Measures: Spending time in the sun increases your risk of skin cancer and early skin aging. To decrease this risk, regularly use a sunscreen with a Broad Spectrum SPF value of 15 or higher and other sun protection measures including:

- limit time in the sun, especially from 10 a.m.-2 p.m.
- wear long-sleeved shirts, pants, hats and sunglasses

Other Information

- protect the product in this container from excessive heat and direct sun

Inactive ingredients

water, glycerin, polyethylene, hydroxyethyl acrylate/sodium acryloyidimethyl taurate copolymer, isohexadecane, polysorbate 60, dimethicone, cetyl alcohol, cetearyl alcohol, cetearyl glucoside, panthenol (pro-vitamin B5), niacinamide, phenoxyethanol, methylparaben, ethylparaben, propylparaben, stearyl alcohol, cyclopentasiloxane, dimethiconol, behenyl alcohol, tocopheryl acetate (vitamin E), DMDM hydantion, benzyl alcohol, PEG-4 dilaurate, stearic acid, PEG-100 stearate, fragrance, disodium EDTA

Package/Label Principal Display Panel

Best Choice® absolute Daily Moisturizer

Broad Spectrum SPF15 Sunscreen

With Vitamin E & Pro-vitamin B5

*Compare to Olay® Complete
All Day UV Moisturizer SPF15 ingredients

4 FL OZ (118 mL)

*This product is not manufactured or distributed by Procter & Gamble, owner of the registered trademark Olay® Complete

PROUDLY DISTRIBUTED BY:
VALU MERCHANDISERS, CO.
KANSAS CITY, KS 66106
100% GUARANTEE
www.awgbrands.com

Manufactured in Israel
1D6267F C1

Carton Label